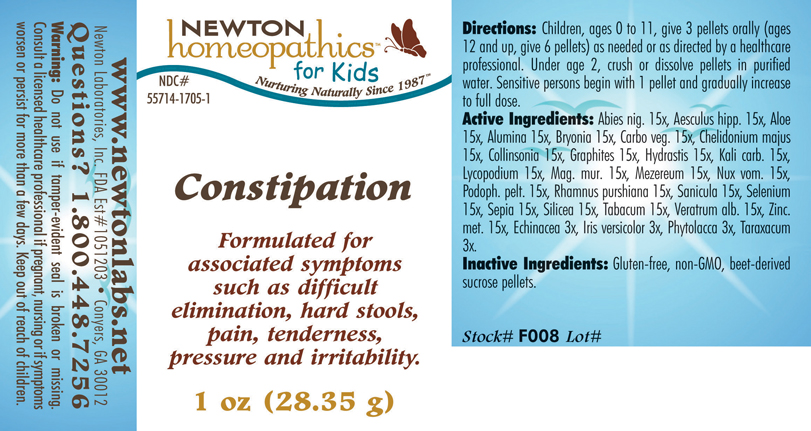 DRUG LABEL: Constipation 
NDC: 55714-1705 | Form: PELLET
Manufacturer: Newton Laboratories, Inc.
Category: homeopathic | Type: HUMAN OTC DRUG LABEL
Date: 20110301

ACTIVE INGREDIENTS: Picea Mariana Resin 15 [hp_X]/1 g; Horse Chestnut 15 [hp_X]/1 g; Aloe 15 [hp_X]/1 g; Aluminum Oxide 15 [hp_X]/1 g; Bryonia Alba Root 15 [hp_X]/1 g; Activated Charcoal 15 [hp_X]/1 g; Chelidonium Majus 15 [hp_X]/1 g; Collinsonia Canadensis Root 15 [hp_X]/1 g; Graphite 15 [hp_X]/1 g; Goldenseal 15 [hp_X]/1 g; Potassium Carbonate 15 [hp_X]/1 g; Lycopodium Clavatum Spore 15 [hp_X]/1 g; Magnesium Chloride 15 [hp_X]/1 g; Daphne Mezereum Bark 15 [hp_X]/1 g; Strychnos Nux-vomica Seed 15 [hp_X]/1 g; Podophyllum 15 [hp_X]/1 g; Frangula Purshiana Bark 15 [hp_X]/1 g; Sanicula Europaea Leaf 15 [hp_X]/1 g; Selenium 15 [hp_X]/1 g; Sepia Officinalis Juice 15 [hp_X]/1 g; Silicon Dioxide 15 [hp_X]/1 g; Tobacco Leaf 15 [hp_X]/1 g; Veratrum Album Root 15 [hp_X]/1 g; Zinc 15 [hp_X]/1 g; Echinacea, Unspecified 3 [hp_X]/1 g; Iris Versicolor Root 3 [hp_X]/1 g; Phytolacca Americana Root 3 [hp_X]/1 g; Taraxacum Officinale 3 [hp_X]/1 g
INACTIVE INGREDIENTS: Sucrose

Constipation

INDICATIONS & USAGE SECTION

Constipation Formulated for associated symptoms such as difficult elimination, hard stools, pain, tenderness, pressure and irritability.

DOSAGE & ADMINISTRATION SECTION

Directions: Children, ages 0 to 11, give 3 pellets orally (ages 12 and up, give 6 pellets) as needed or as directed by a healthcare professional. Under age 2, crush or dissolve pellets in purified water. Sensitive persons begin with 1 pellet and gradually increase to full dose.

OTC - ACTIVE INGREDIENT SECTION

Abies nig. 15x, Aesculus hipp. 15x, Aloe 15x, Alumina 15x, Bryonia 15x, Carbo veg. 15x, Chelidonium majus 15x, Collinsonia 15x, Graphites 15x, Hydrastis 15x, Kali carb. 15x, Lycopodium 15x, Mag. mur. 15x, Mezereum 15x, Nux vom. 15x, Podoph. pelt. 15x, Rhamnus purshiana 15x, Sanicula 15x, Selenium 15x, Sepia 15x, Silicea 15x, Tabacum 15x, Veratrum alb. 15x, Zinc.met. 15x, Echinacea 3x, Iris versicolor 3x, Phytolacca 3x, Taraxacum 3x.

OTC - PURPOSE SECTION

Formulated for associated symptoms such as difficult elimination, hard stools, pain, tenderness, pressure and irritability.

INACTIVE INGREDIENT SECTION

Inactive Ingredients: Gluten-free, non-GMO, beet-derived sucrose pellets.

QUESTIONS SECTION

www.newtonlabs.net Newton Laboratories, Inc. FDA Est # 1051203 - Conyers, GA 30012
Questions? 1.800.448.7256

WARNINGS SECTION

Warning: Do not use if tamper - evident seal is broken or missing. Consult a licensed healthcare professional if pregnant, nursing or if symptoms worsen or persist for more than a few days. Keep out of reach of children.

OTC - PREGNANCY OR BREAST FEEDING SECTION

Consult a licensed healthcare professional if pregnant, nursing or if symptoms worsen or persist for more than a few days.

OTC - KEEP OUT OF REACH OF CHILDREN SECTION

Keep out of reach of children.